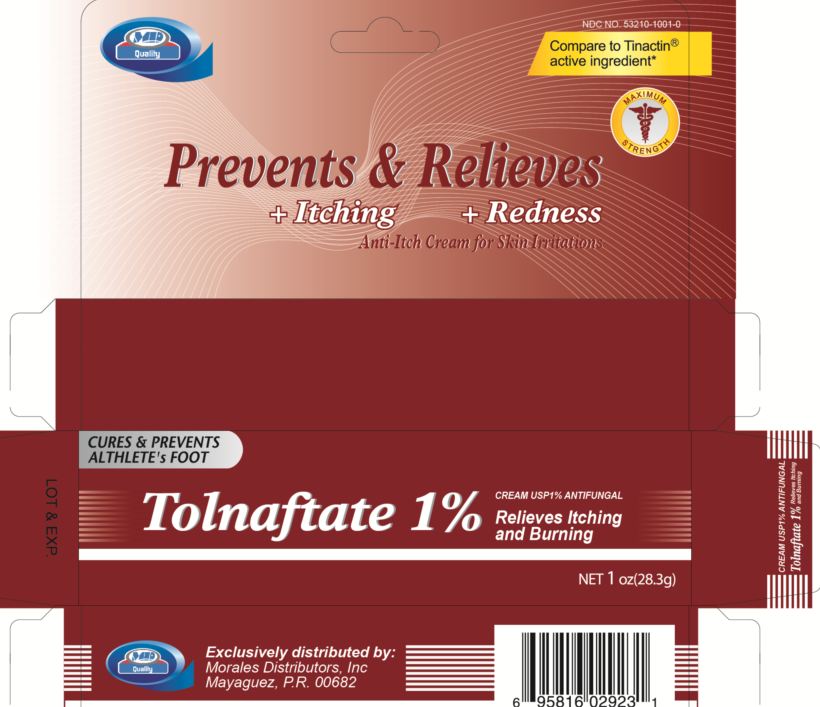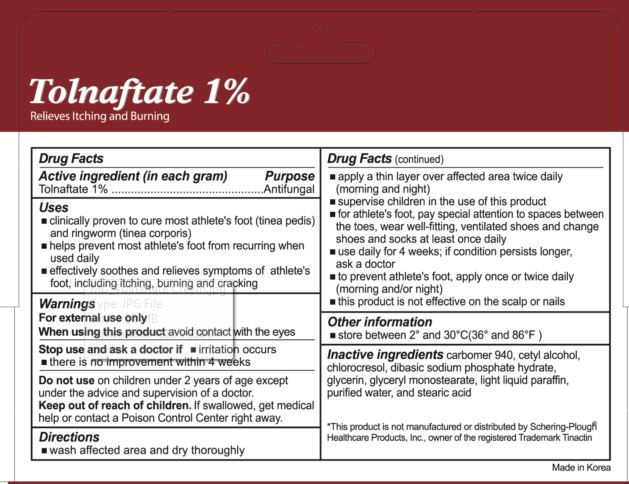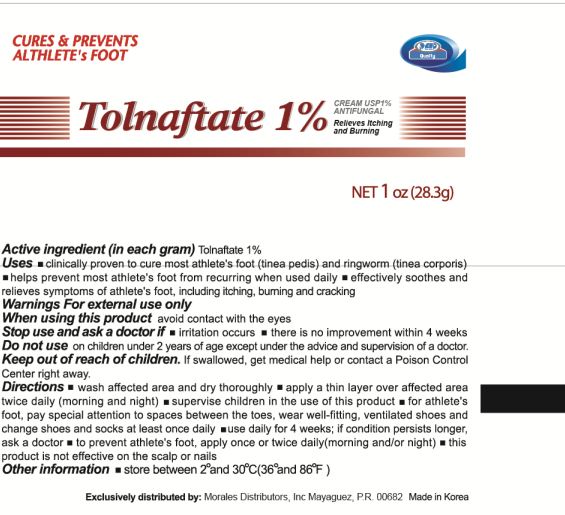 DRUG LABEL: Tolnaftate
                
                
NDC: 53210-1001 | Form: CREAM
Manufacturer: Morales Distributors, Inc.
Category: otc | Type: HUMAN OTC DRUG LABEL
Date: 20120928

ACTIVE INGREDIENTS: TOLNAFTATE 1 g/100 g
INACTIVE INGREDIENTS: CARBOMER HOMOPOLYMER TYPE C; CETYL ALCOHOL; CHLOROCRESOL; GLYCERIN; GLYCERYL MONOSTEARATE; LIGHT MINERAL OIL; WATER; STEARIC ACID

Tolnaftate 1 percent

Active ingredient (in each gram)

Tolnaftate 1 percent

Purpose

Antifungal

Uses

- clinically proven to cure most athlete's foot (tinea pedis) and ringworm (tinea corporis)
- helps prevent most athlete's foot from recurring when used daily
- effectively soothes and relieves symptoms of athlete's foot, including itching, burning and cracking

Warnings

For external use only

When using this product avoid contact with the eyes

Stop use and ask a doctor if

- irritation occurs
- there is no improvement within 4 weeks

Do not use

on children under 2 years of age except under the advice and supervision of a doctor.

Keep out of reach of children.

If swallowed, get medical help or contact a Poison Control Center right away.

Directions

- wash affected area and dry thoroughly
- apply a thin layer over affected area twice daily (morning and night)
- supervise children in the use of this product
- for athlete's foot, pay special attentional to spaces between the toes, wear well-fitting, ventilated shoes and change shoes and socks at least once daily
- use daily for 4 weeks; if condition persists longer ask a doctor
- to prevent athlete's foot, apply once or twice daily (morning and night)
- this product is not effective on the scalp or nails

Other information

store between 2 degrees and 30 degrees Celsius (36 degrees and 86 degrees Fahrenheit)

Inactive ingredients

carbomer 940, cetyl alcohol, chlorocresol, dibasic sodium phosphate hydrate, glycerin, glyceryl monostearate, light liquid paraffin, purified water, and stearic acid

Package label

NDC NO. 53210-1001-0
Tolnafate 1 percent
Cream USP 1 percent Antifungal

Relieves Itching and Burning

Cures and Prevents Athlete's Foot

Prevents and Relieves Itching and Redness

Anti-Itch Cream for Skin Irritations

Compare to Tinactin (R) active ingredient
This product is n ot manufactured or distributed by Schering-Plough Healthcare Products, Inc. owner of the registered Trademark Tinactin

Maximum Strength

Net 1 oz(28.3g)

Exclusively distributed by:
Morales Distributors, Inc
Mayaguez, P.R. 00682

Made in Korea